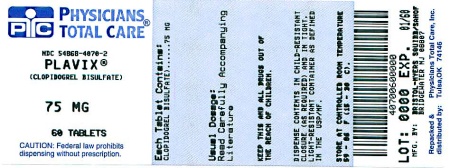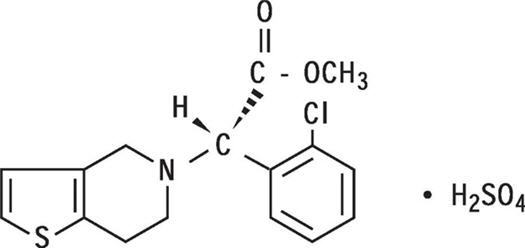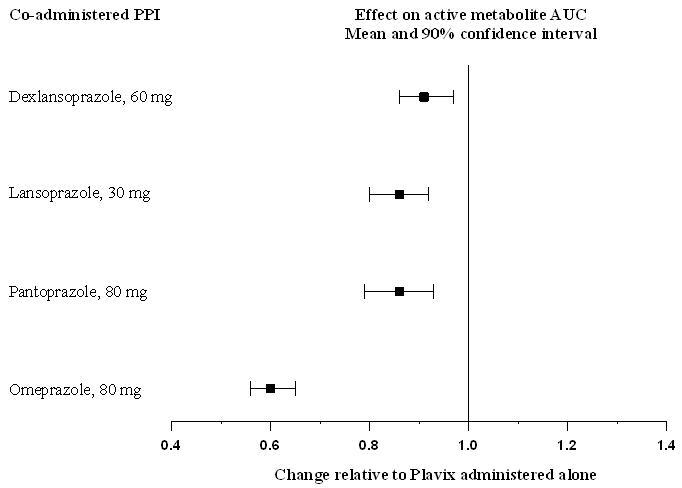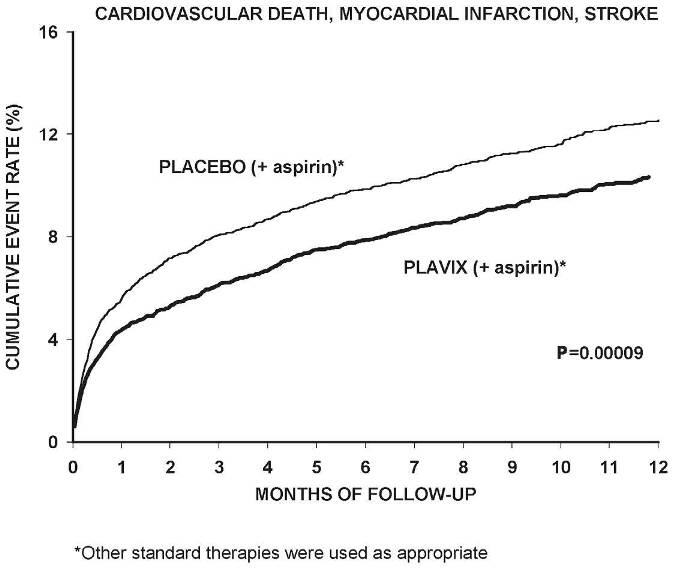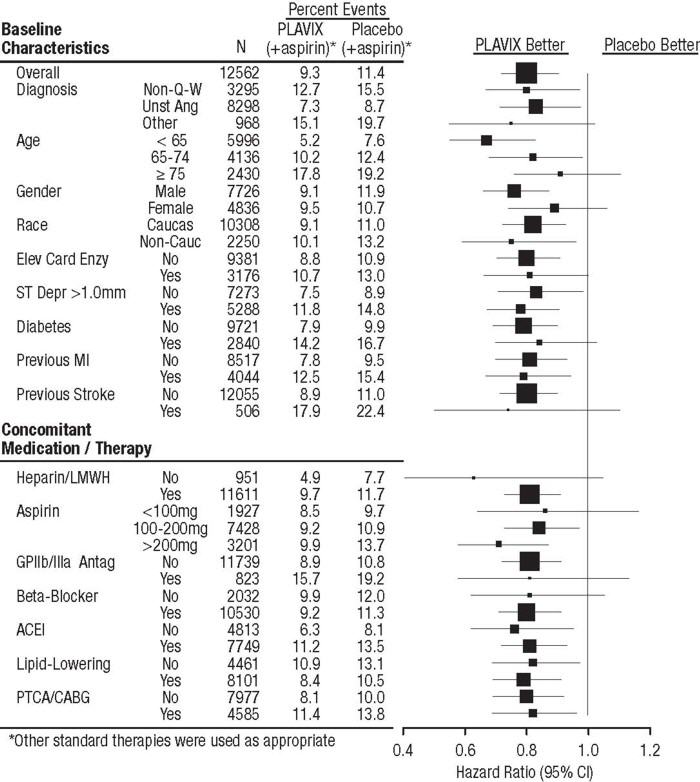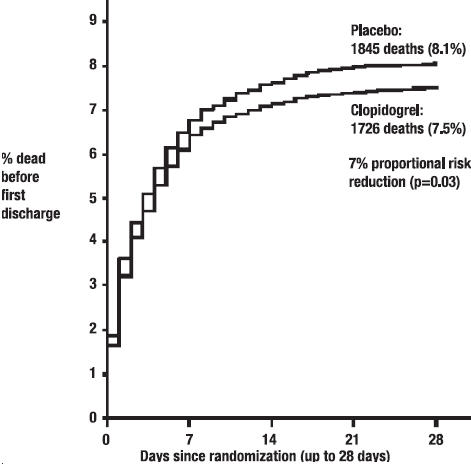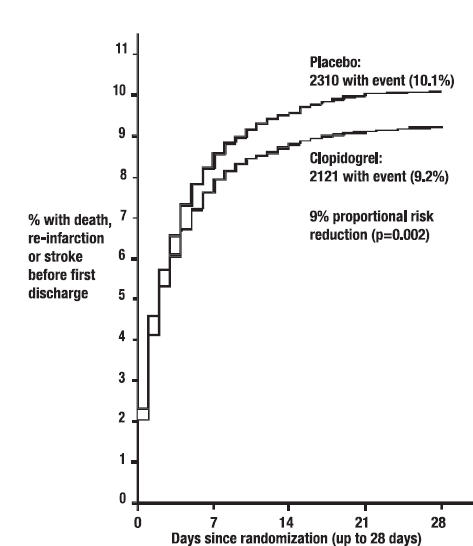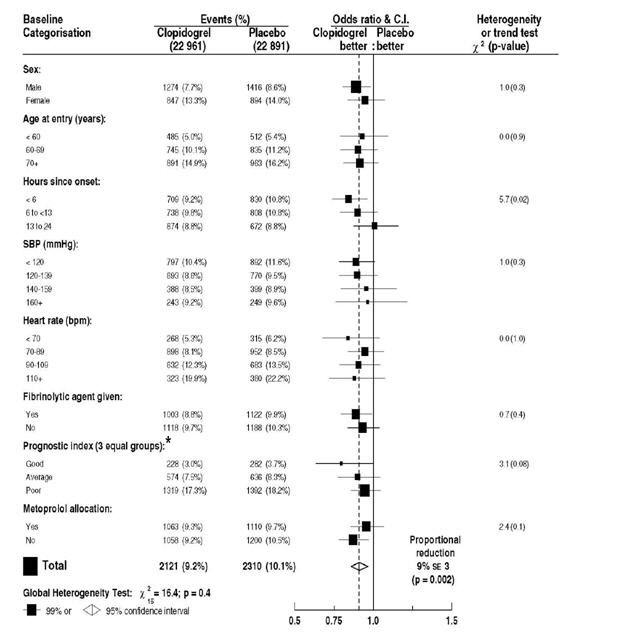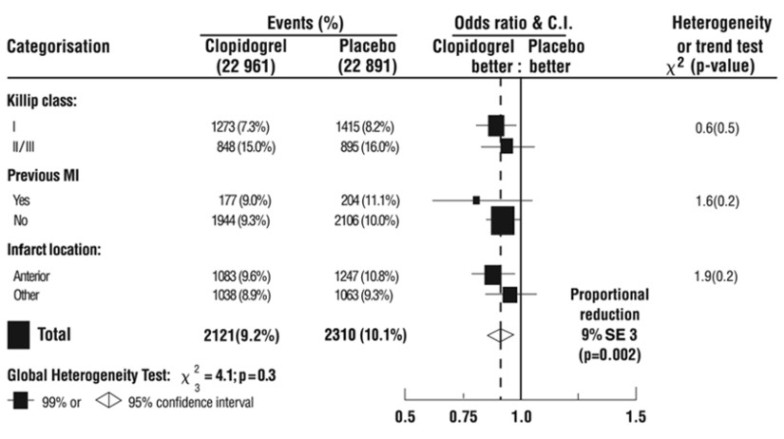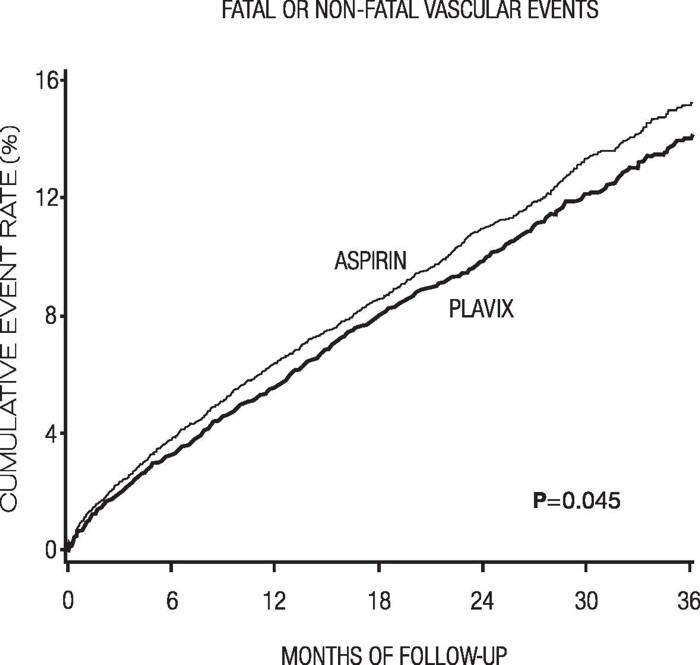 DRUG LABEL: Plavix
NDC: 54868-4070 | Form: TABLET, FILM COATED
Manufacturer: Physicians Total Care, Inc.
Category: prescription | Type: HUMAN PRESCRIPTION DRUG LABEL
Date: 20120112

ACTIVE INGREDIENTS: clopidogrel bisulfate 75 mg/1 1
INACTIVE INGREDIENTS: castor oil; hydroxypropyl cellulose; mannitol; cellulose, microcrystalline; polyethylene glycol 6000; ferric oxide red; lactose monohydrate; titanium dioxide; triacetin; carnauba wax

HIGHLIGHTS OF PRESCRIBING INFORMATION

These highlights do not include all the information needed to use
PLAVIX safely and effectively. See full prescribing information for
PLAVIX.
PLAVIX (clopidogrel bisulfate) tablets
Initial U.S. Approval: 1997

WARNING: DIMINISHED EFFECTIVENESS IN POOR METABOLIZERS

See full prescribing information for complete boxed warning.

- Effectiveness of Plavix depends on activation to an active metabolite by the cytochrome P450 (CYP) system, principally CYP2C19. (5.1)
- Poor metabolizers treated with Plavix at recommended doses exhibit higher cardiovascular event rates following acute coronary syndrome (ACS) or percutaneous coronary intervention (PCI) than patients with normal CYP2C19 function. (12.5)
- Tests are available to identify a patient's CYP2C19 genotype and can be used as an aid in determining therapeutic strategy. (12.5)
- Consider alternative treatment or treatment strategies in patients identified as CYP2C19 poor metabolizers. (2.3, 5.1)

RECENT MAJOR CHANGES

Dosage and Administration (2.4) | 12/2011
Warnings and Precautions (5.1) | 12/2011

1 INDICATIONS AND USAGE

Plavix is a P2Y12 platelet inhibitor indicated for:

- Acute coronary syndrome
  - For patients with non-ST-segment elevation ACS [unstable angina (UA)/non-ST-elevation myocardial infarction (NSTEMI)] including patients who are to be managed medically and those who are to be managed with coronary revascularization, Plavix has been shown to decrease the rate of a combined endpoint of cardiovascular death, myocardial infarction (MI), or stroke as well as the rate of a combined endpoint of cardiovascular death, MI, stroke, or refractory ischemia. (1.1)
  - For patients with ST-elevation myocardial infarction (STEMI), Plavix has been shown to reduce the rate of death from any cause and the rate of a combined endpoint of death, re-infarction, or stroke. The benefit for patients who undergo primary PCI is unknown. (1.1)
- Recent myocardial infarction (MI), recent stroke, or established peripheral arterial disease. Plavix has been shown to reduce the combined endpoint of new ischemic stroke (fatal or not), new MI (fatal or not), and other vascular death. (1.2)

2 DOSAGE AND ADMINISTRATION

- Acute coronary syndrome (2.1)
  - Non-ST-segment elevation ACS (UA/NSTEMI): 300 mg loading dose followed by 75 mg once daily, in combination with aspirin (75–325 mg once daily)
  - STEMI: 75 mg once daily, in combination with aspirin (75–325 mg once daily), with or without a loading dose and with or without thrombolytics
- Recent MI, recent stroke, or established peripheral arterial disease: 75 mg once daily (2.2)

3 DOSAGE FORMS AND STRENGTHS

Tablets: 75 mg, 300 mg (3)

4 CONTRAINDICATIONS

- Active pathological bleeding, such as peptic ulcer or intracranial hemorrhage (4.1)
- Hypersensitivity to clopidogrel or any component of the product (4.2)

5 WARNINGS AND PRECAUTIONS

- Reduced effectiveness in impaired CYP2C19 function: Avoid concomitant use with omeprazole or esomeprazole. (5.1)
- Bleeding: Plavix increases risk of bleeding. Discontinue 5 days prior to elective surgery. (5.2)
- Discontinuation of Plavix: Premature discontinuation increases risk of cardiovascular events. (5.3)
- Recent transient ischemic attack or stroke: Combination use of Plavix and aspirin in these patients was not shown to be more effective than Plavix alone, but was shown to increase major bleeding. (5.4)
- Thrombotic thrombocytopenic purpura (TTP): TTP has been reported with Plavix, including fatal cases. (5.5)

6 ADVERSE REACTIONS

Bleeding, including life-threatening and fatal bleeding, is the most commonly reported adverse reaction. (6.1)

To report SUSPECTED ADVERSE REACTIONS, contact Bristol-Myers Squibb/Sanofi Pharmaceuticals Partnership at 1-800-633-1610 or FDA at 1-800-FDA-1088 or www.fda.gov/medwatch.

7 DRUG INTERACTIONS

- Nonsteroidal anti-inflammatory drugs (NSAIDs): Combination use increases risk of gastrointestinal bleeding. (7.2)
- Warfarin: Combination use increases risk of bleeding. (7.3)

8 USE IN SPECIFIC POPULATIONS

Nursing mothers: Discontinue drug or nursing, taking into consideration importance of drug to mother. (8.3)

FULL PRESCRIBING INFORMATION

WARNING: DIMINISHED EFFECTIVENESS IN POOR METABOLIZERS

The effectiveness of Plavix is dependent on its activation to an active metabolite by the cytochrome P450 (CYP) system, principally CYP2C19 [see Warnings and Precautions (5.1)]. Plavix at recommended doses forms less of that metabolite and has a smaller effect on platelet function in patients who are CYP2C19 poor metabolizers. Poor metabolizers with acute coronary syndrome or undergoing percutaneous coronary intervention treated with Plavix at recommended doses exhibit higher cardiovascular event rates than do patients with normal CYP2C19 function. Tests are available to identify a patient's CYP2C19 genotype; these tests can be used as an aid in determining therapeutic strategy [see Clinical Pharmacology (12.5)]. Consider alternative treatment or treatment strategies in patients identified as CYP2C19 poor metabolizers [see Dosage and Administration (2.3)].

1 INDICATIONS AND USAGE

1.1 Acute Coronary Syndrome (ACS)

- For patients with non-ST-segment elevation ACS [unstable angina (UA)/non-ST-elevation myocardial infarction (NSTEMI)], including patients who are to be managed medically and those who are to be managed with coronary revascularization, Plavix has been shown to decrease the rate of a combined endpoint of cardiovascular death, myocardial infarction (MI), or stroke as well as the rate of a combined endpoint of cardiovascular death, MI, stroke, or refractory ischemia.
- For patients with ST-elevation myocardial infarction (STEMI), Plavix has been shown to reduce the rate of death from any cause and the rate of a combined endpoint of death, re-infarction, or stroke. The benefit for patients who undergo primary percutaneous coronary intervention is unknown.

The optimal duration of Plavix therapy in ACS is unknown.

1.2 Recent MI, Recent Stroke, or Established Peripheral Arterial Disease

For patients with a history of recent myocardial infarction (MI), recent stroke, or established peripheral arterial disease, Plavix has been shown to reduce the rate of a combined endpoint of new ischemic stroke (fatal or not), new MI (fatal or not), and other vascular death.

2 DOSAGE AND ADMINISTRATION

2.1 Acute Coronary Syndrome

Plavix can be administered with or without food [see Clinical Pharmacology (12.3)].

- For patients with non-ST-elevation ACS (UA/NSTEMI), initiate Plavix with a single 300 mg oral loading dose and then continue at 75 mg once daily. Initiate aspirin (75–325 mg once daily) and continue in combination with Plavix [see Clinical Studies (14.1)].
- For patients with STEMI, the recommended dose of Plavix is 75 mg once daily orally, administered in combination with aspirin (75–325 mg once daily), with or without thrombolytics. Plavix may be initiated with or without a loading dose [see Clinical Studies (14.1)].

2.2 Recent MI, Recent Stroke, or Established Peripheral Arterial Disease

The recommended daily dose of Plavix is 75 mg once daily orally, with or without food [see Clinical Pharmacology (12.3)].

2.3 CYP2C19 Poor Metabolizers

CYP2C19 poor metabolizer status is associated with diminished antiplatelet response to clopidogrel. Although a higher dose regimen in poor metabolizers increases antiplatelet response [see Clinical Pharmacology (12.5)], an appropriate dose regimen for this patient population has not been established.

2.4 Use with Proton Pump Inhibitors (PPI)

Avoid using omeprazole or esomeprazole with Plavix. Omeprazole and esomeprazole significantly reduce the antiplatelet activity of Plavix. When concomitant administration of a PPI is required, consider using another acid-reducing agent with minimal or no CYP2C19 inhibitory effect on the formation of clopidogrel active metabolite [see Warnings and Precautions (5.1), Drug Interactions (7.1) and Clinical Pharmacology (12.3)].

3 DOSAGE FORMS AND STRENGTHS

- 75 mg tablets: Pink, round, biconvex, film-coated tablets debossed with "75" on one side and "1171" on the other
- 300 mg tablets: Pink, oblong, film-coated tablets debossed with "300" on one side and "1332" on the other

4 CONTRAINDICATIONS

4.1 Active Bleeding

Plavix is contraindicated in patients with active pathological bleeding such as peptic ulcer or intracranial hemorrhage.

4.2 Hypersensitivity

Plavix is contraindicated in patients with hypersensitivity (e.g., anaphylaxis) to clopidogrel or any component of the product [see Adverse Reactions (6.2)].

5 WARNINGS AND PRECAUTIONS

5.1 Diminished Antiplatelet Activity Due to Impaired CYP2C19 Function

Clopidogrel is a prodrug. Inhibition of platelet aggregation by clopidogrel is achieved through an active metabolite. The metabolism of clopidogrel to its active metabolite can be impaired by genetic variations in CYP2C19 [see Boxed Warning] and by concomitant medications that interfere with CYP2C19.

Proton Pump Inhibitors

Avoid concomitant use of Plavix with omeprazole or esomeprazole because both significantly reduce the antiplatelet activity of Plavix [see Drug Interactions (7.1) and Dosage and Administration (2.4)].

5.2 General Risk of Bleeding

Thienopyridines, including Plavix, increase the risk of bleeding. If a patient is to undergo surgery and an antiplatelet effect is not desired, discontinue Plavix five days prior to surgery. In patients who stopped therapy more than five days prior to CABG the rates of major bleeding were similar (event rate 4.4% Plavix + aspirin; 5.3% placebo + aspirin). In patients who remained on therapy within five days of CABG, the major bleeding rate was 9.6% for Plavix + aspirin, and 6.3% for placebo + aspirin.

Thienopyridines inhibit platelet aggregation for the lifetime of the platelet (7–10 days), so withholding a dose will not be useful in managing a bleeding event or the risk of bleeding associated with an invasive procedure. Because the half-life of clopidogrel's active metabolite is short, it may be possible to restore hemostasis by administering exogenous platelets; however, platelet transfusions within 4 hours of the loading dose or 2 hours of the maintenance dose may be less effective.

5.3 Discontinuation of Plavix

Avoid lapses in therapy, and if Plavix must be temporarily discontinued, restart as soon as possible. Premature discontinuation of Plavix may increase the risk of cardiovascular events.

5.4 Patients with Recent Transient Ischemic Attack (TIA) or Stroke

In patients with recent TIA or stroke who are at high risk for recurrent ischemic events, the combination of aspirin and Plavix has not been shown to be more effective than Plavix alone, but the combination has been shown to increase major bleeding.

5.5 Thrombotic Thrombocytopenic Purpura (TTP)

TTP, sometimes fatal, has been reported following use of Plavix, sometimes after a short exposure (<2 weeks). TTP is a serious condition that requires urgent treatment including plasmapheresis (plasma exchange). It is characterized by thrombocytopenia, microangiopathic hemolytic anemia (schistocytes [fragmented RBCs] seen on peripheral smear), neurological findings, renal dysfunction, and fever [see Adverse Reactions (6.2)].

6 ADVERSE REACTIONS

The following serious adverse reactions are discussed below and elsewhere in the labeling:

- Bleeding [see Warnings and Precautions (5.2)]
- Thrombotic thrombocytopenic purpura [see Warnings and Precautions (5.5)]

6.1 Clinical Studies Experience

Because clinical trials are conducted under widely varying conditions and durations of follow up, adverse reaction rates observed in the clinical trials of a drug cannot be directly compared to rates in the clinical trials of another drug and may not reflect the rates observed in practice.

Plavix has been evaluated for safety in more than 54,000 patients, including over 21,000 patients treated for 1 year or more. The clinically important adverse reactions observed in trials comparing Plavix plus aspirin to placebo plus aspirin and trials comparing Plavix alone to aspirin alone are discussed below.

Bleeding

CURE

In CURE, Plavix use with aspirin was associated with an increase in major bleeding (primarily gastrointestinal and at puncture sites) compared to placebo with aspirin (see Table 1). The incidence of intracranial hemorrhage (0.1%) and fatal bleeding (0.2%) were the same in both groups. Other bleeding events that were reported more frequently in the clopidogrel group were epistaxis, hematuria, and bruise.

The overall incidence of bleeding is described in Table 1.

Table 1: CURE Incidence of Bleeding Complications (% patients)
Event | Plavix (+ aspirin) [Other standard therapies were used as appropriate.] | Placebo (+ aspirin)
 | (n=6259) | (n=6303)
Major bleeding [Life-threatening and other major bleeding.] | 3.7 [Major bleeding event rate for Plavix + aspirin was dose-dependent on aspirin: <100 mg = 2.6%; 100–200 mg = 3.5%; >200 mg = 4.9% Major bleeding event rates for Plavix + aspirin by age were: <65 years = 2.5%, ≥65 to <75 years = 4.1%, ≥75 years = 5.9%] | 2.7 [Major bleeding event rate for placebo + aspirin was dose-dependent on aspirin: <100 mg = 2.0%; 100–200 mg = 2.3%; >200 mg = 4.0% Major bleeding event rates for placebo + aspirin by age were: <65 years = 2.1%, ≥65 to <75 years = 3.1%, ≥75 years = 3.6%]
Life-threatening bleeding | 2.2 | 1.8
Fatal | 0.2 | 0.2
5 g/dL hemoglobin drop | 0.9 | 0.9
Requiring surgical intervention | 0.7 | 0.7
Hemorrhagic strokes | 0.1 | 0.1
Requiring inotropes | 0.5 | 0.5
Requiring transfusion (≥4 units) | 1.2 | 1.0
Other major bleeding | 1.6 | 1.0
Significantly disabling | 0.4 | 0.3
Intraocular bleeding with significant loss of vision | 0.05 | 0.03
Requiring 2–3 units of blood | 1.3 | 0.9
Minor bleeding [Led to interruption of study medication.] | 5.1 | 2.4

Ninety-two percent (92%) of the patients in the CURE study received heparin or low molecular weight heparin (LMWH), and the rate of bleeding in these patients was similar to the overall results.

COMMIT

In COMMIT, similar rates of major bleeding were observed in the Plavix and placebo groups, both of which also received aspirin (see Table 2).

Table 2: Incidence of Bleeding Events in COMMIT (% patients)
Type of bleeding | Plavix (+ aspirin) (n=22961) | Placebo (+ aspirin) (n=22891) | p-value
Major [Major bleeds were cerebral bleeds or non-cerebral bleeds thought to have caused death or that required transfusion.] noncerebral or cerebral bleeding [The relative rate of major noncerebral or cerebral bleeding was independent of age. Event rates for Plavix + aspirin by age were: <60 years = 0.3%, ≥60 to <70 years = 0.7%, ≥70 years = 0.8%. Event rates for placebo + aspirin by age were: <60 years = 0.4%, ≥60 to <70 years = 0.6%, ≥70 years = 0.7%.] | 0.6 | 0.5 | 0.59
Major noncerebral | 0.4 | 0.3 | 0.48
Fatal | 0.2 | 0.2 | 0.90
Hemorrhagic stroke | 0.2 | 0.2 | 0.91
Fatal | 0.2 | 0.2 | 0.81
Other noncerebral bleeding (non-major) | 3.6 | 3.1 | 0.005
Any noncerebral bleeding | 3.9 | 3.4 | 0.004

CAPRIE (Plavix vs. Aspirin)

In CAPRIE, gastrointestinal hemorrhage occurred at a rate of 2.0% in those taking Plavix vs. 2.7% in those taking aspirin; bleeding requiring hospitalization occurred in 0.7% and 1.1%, respectively. The incidence of intracranial hemorrhage was 0.4% for Plavix compared to 0.5% for aspirin.

Other bleeding events that were reported more frequently in the Plavix group were epistaxis and hematoma.

Other Adverse Events

In CURE and CHARISMA, which compared Plavix plus aspirin to aspirin alone, there was no difference in the rate of adverse events (other than bleeding) between Plavix and placebo.

In CAPRIE, which compared Plavix to aspirin, pruritus was more frequently reported in those taking Plavix. No other difference in the rate of adverse events (other than bleeding) was reported.

6.2 Postmarketing Experience

The following adverse reactions have been identified during post-approval use of Plavix. Because these reactions are reported voluntarily from a population of an unknown size, it is not always possible to reliably estimate their frequency or establish a causal relationship to drug exposure.

- Blood and lymphatic system disorders: Agranulocytosis, aplastic anemia/pancytopenia, thrombotic thrombocytopenic purpura (TTP)
- Eye disorders: Eye (conjunctival, ocular, retinal) bleeding
- Gastrointestinal disorders: Gastrointestinal and retroperitoneal hemorrhage with fatal outcome, colitis (including ulcerative or lymphocytic colitis), pancreatitis, stomatitis, gastric/duodenal ulcer, diarrhea
- General disorders and administration site condition: Fever, hemorrhage of operative wound
- Hepato-biliary disorders: Acute liver failure, hepatitis (non-infectious), abnormal liver function test
- Immune system disorders: Hypersensitivity reactions, anaphylactoid reactions, serum sickness
- Musculoskeletal, connective tissue and bone disorders: Musculoskeletal bleeding, myalgia, arthralgia, arthritis
- Nervous system disorders: Taste disorders, fatal intracranial bleeding, headache
- Psychiatric disorders: Confusion, hallucinations
- Respiratory, thoracic and mediastinal disorders: Bronchospasm, interstitial pneumonitis, respiratory tract bleeding
- Renal and urinary disorders: Increased creatinine levels
- Skin and subcutaneous tissue disorders: Maculopapular or erythematous rash, urticaria, bullous dermatitis, eczema, toxic epidermal necrolysis, Stevens-Johnson syndrome, angioedema, erythema multiforme, skin bleeding, lichen planus, generalized pruritus
- Vascular disorders: Vasculitis, hypotension

7 DRUG INTERACTIONS

7.1 CYP2C19 Inhibitors

Clopidogrel is metabolized to its active metabolite in part by CYP2C19. Concomitant use of certain drugs that inhibit the activity of this enzyme results in reduced plasma concentrations of the active metabolite of clopidogrel and a reduction in platelet inhibition [see Warnings and Precautions (5.1) and Dosage and Administration (2.4)].

Proton Pump Inhibitors (PPI)

Avoid concomitant use of Plavix with omeprazole or esomeprazole. In clinical studies, omeprazole was shown to reduce the antiplatelet activity of Plavix when given concomitantly or 12 hours apart. A higher dose regimen of clopidogrel concomitantly administered with omeprazole increases antiplatelet response; an appropriate dose regimen has not been established. A similar reduction in antiplatelet activity was observed with esomeprazole when given concomitantly with Plavix. Consider using another acid-reducing agent with minimal or no CYP2C19 inhibitory effect on the formation of clopidogrel active metabolite. Dexlansoprazole, lansoprazole and pantoprazole had less effect on the antiplatelet activity of Plavix than did omeprazole or esomeprazole [see Dosage and Administration (2.4), Warnings and Precautions (5.1) and Clinical Pharmacology (12.3)].

7.2 Nonsteroidal Anti-Inflammatory Drugs (NSAIDs)

Coadministration of Plavix and NSAIDs increases the risk of gastrointestinal bleeding.

7.3 Warfarin (CYP2C9 Substrates)

Although the administration of clopidogrel 75 mg per day did not modify the pharmacokinetics of S-warfarin (a CYP2C9 substrate) or INR in patients receiving long-term warfarin therapy, coadministration of Plavix with warfarin increases the risk of bleeding because of independent effects on hemostasis.

However, at high concentrations in vitro, clopidogrel inhibits CYP2C9.

8 USE IN SPECIFIC POPULATIONS

8.1 Pregnancy

Pregnancy Category B

Reproduction studies performed in rats and rabbits at doses up to 500 and 300 mg/kg/day, respectively (65 and 78 times the recommended daily human dose, respectively, on a mg/m^2 basis), revealed no evidence of impaired fertility or fetotoxicity due to clopidogrel. There are, however, no adequate and well-controlled studies in pregnant women. Because animal reproduction studies are not always predictive of a human response, Plavix should be used during pregnancy only if clearly needed.

8.3 Nursing Mothers

Studies in rats have shown that clopidogrel and/or its metabolites are excreted in the milk. It is not known whether this drug is excreted in human milk. Because many drugs are excreted in human milk and because of the potential for serious adverse reactions in nursing infants from clopidogrel, a decision should be made whether to discontinue nursing or to discontinue the drug, taking into account the importance of the drug to the mother.

8.4 Pediatric Use

Safety and effectiveness in pediatric populations have not been established.

A randomized, placebo-controlled trial (CLARINET) did not demonstrate a clinical benefit of clopidogrel in neonates and infants with cyanotic congenital heart disease palliated with a systemic-to-pulmonary arterial shunt. Possible factors contributing to this outcome were the dose of clopidogrel, the concomitant administration of aspirin and the late initiation of therapy following shunt palliation. It cannot be ruled out that a trial with a different design would demonstrate a clinical benefit in this patient population.

8.5 Geriatric Use

Of the total number of subjects in the CAPRIE and CURE controlled clinical studies, approximately 50% of patients treated with Plavix were 65 years of age and older, and 15% were 75 years and older. In COMMIT, approximately 58% of the patients treated with Plavix were 60 years and older, 26% of whom were 70 years and older.

The observed risk of bleeding events with Plavix plus aspirin versus placebo plus aspirin by age category is provided in Table 1 and Table 2 for the CURE and COMMIT trials, respectively [see Adverse Reactions (6.1)]. No dosage adjustment is necessary in elderly patients.

8.6 Renal Impairment

Experience is limited in patients with severe and moderate renal impairment [see Clinical Pharmacology (12.2)].

8.7 Hepatic Impairment

No dosage adjustment is necessary in patients with hepatic impairment [see Clinical Pharmacology (12.2)].

10 OVERDOSAGE

Platelet inhibition by Plavix is irreversible and will last for the life of the platelet. Overdose following clopidogrel administration may result in bleeding complications. A single oral dose of clopidogrel at 1500 or 2000 mg/kg was lethal to mice and to rats and at 3000 mg/kg to baboons. Symptoms of acute toxicity were vomiting, prostration, difficult breathing, and gastrointestinal hemorrhage in animals.

Based on biological plausibility, platelet transfusion may restore clotting ability.

11 DESCRIPTION

Plavix (clopidogrel bisulfate) is a thienopyridine class inhibitor of P2Y12 ADP platelet receptors. Chemically it is methyl (+)-(S)-α-(2-chlorophenyl)-6,7-dihydrothieno[3,2-c]pyridine-5(4H)-acetate sulfate (1:1). The empirical formula of clopidogrel bisulfate is C16H16ClNO2S•H2SO4 and its molecular weight is 419.9.

The structural formula is as follows:

Clopidogrel bisulfate is a white to off-white powder. It is practically insoluble in water at neutral pH but freely soluble at pH 1. It also dissolves freely in methanol, dissolves sparingly in methylene chloride, and is practically insoluble in ethyl ether. It has a specific optical rotation of about +56°.

Plavix for oral administration is provided as either pink, round, biconvex, debossed, film-coated tablets containing 97.875 mg of clopidogrel bisulfate which is the molar equivalent of 75 mg of clopidogrel base or pink, oblong, debossed film-coated tablets containing 391.5 mg of clopidogrel bisulfate which is the molar equivalent of 300 mg of clopidogrel base.

Each tablet contains hydrogenated castor oil, hydroxypropylcellulose, mannitol, microcrystalline cellulose and polyethylene glycol 6000 as inactive ingredients. The pink film coating contains ferric oxide, hypromellose 2910, lactose monohydrate, titanium dioxide and triacetin. The tablets are polished with Carnauba wax.

12 CLINICAL PHARMACOLOGY

12.1 Mechanism of Action

Clopidogrel is an inhibitor of platelet activation and aggregation through the irreversible binding of its active metabolite to the P2Y12 class of ADP receptors on platelets.

12.2 Pharmacodynamics

Clopidogrel must be metabolized by CYP450 enzymes to produce the active metabolite that inhibits platelet aggregation. The active metabolite of clopidogrel selectively inhibits the binding of adenosine diphosphate (ADP) to its platelet P2Y12 receptor and the subsequent ADP-mediated activation of the glycoprotein GPIIb/IIIa complex, thereby inhibiting platelet aggregation. This action is irreversible. Consequently, platelets exposed to clopidogrel's active metabolite are affected for the remainder of their lifespan (about 7 to 10 days). Platelet aggregation induced by agonists other than ADP is also inhibited by blocking the amplification of platelet activation by released ADP.

Dose-dependent inhibition of platelet aggregation can be seen 2 hours after single oral doses of Plavix. Repeated doses of 75 mg Plavix per day inhibit ADP-induced platelet aggregation on the first day, and inhibition reaches steady state between Day 3 and Day 7. At steady state, the average inhibition level observed with a dose of 75 mg Plavix per day was between 40% and 60%. Platelet aggregation and bleeding time gradually return to baseline values after treatment is discontinued, generally in about 5 days.

Geriatric Patients

Elderly (≥75 years) and young healthy subjects had similar effects on platelet aggregation.

Renally-Impaired Patients

After repeated doses of 75 mg Plavix per day, patients with severe renal impairment (creatinine clearance from 5 to 15 mL/min) and moderate renal impairment (creatinine clearance from 30 to 60 mL/min) showed low (25%) inhibition of ADP-induced platelet aggregation.

Hepatically-Impaired Patients

After repeated doses of 75 mg Plavix per day for 10 days in patients with severe hepatic impairment, inhibition of ADP-induced platelet aggregation was similar to that observed in healthy subjects.

Gender

In a small study comparing men and women, less inhibition of ADP-induced platelet aggregation was observed in women.

12.3 Pharmacokinetics

Clopidogrel is a prodrug and is metabolized to a pharmacologically active metabolite and inactive metabolites.

Absorption

After single and repeated oral doses of 75 mg per day, clopidogrel is rapidly absorbed. Absorption is at least 50%, based on urinary excretion of clopidogrel metabolites.

Effect of Food

Plavix can be administered with or without food. In a study in healthy male subjects when Plavix 75 mg per day was given with a standard breakfast, mean inhibition of ADP-induced platelet aggregation was reduced by less than 9%. The active metabolite AUC0–24 was unchanged in the presence of food, while there was a 57% decrease in active metabolite Cmax. Similar results were observed when a Plavix 300 mg loading dose was administered with a high-fat breakfast.

Metabolism

Clopidogrel is extensively metabolized by two main metabolic pathways: one mediated by esterases and leading to hydrolysis into an inactive carboxylic acid derivative (85% of circulating metabolites) and one mediated by multiple cytochrome P450 enzymes. Cytochromes first oxidize clopidogrel to a 2-oxo-clopidogrel intermediate metabolite. Subsequent metabolism of the 2-oxo-clopidogrel intermediate metabolite results in formation of the active metabolite, a thiol derivative of clopidogrel. This metabolic pathway is mediated by CYP2C19, CYP3A, CYP2B6 and CYP1A2. The active thiol metabolite binds rapidly and irreversibly to platelet receptors, thus inhibiting platelet aggregation for the lifespan of the platelet.

The Cmax of the active metabolite is twice as high following a single 300 mg clopidogrel loading dose as it is after four days of 75 mg maintenance dose. Cmax occurs approximately 30 to 60 minutes after dosing. In the 75 to 300 mg dose range, the pharmacokinetics of the active metabolite deviates from dose proportionality: increasing the dose by a factor of four results in 2.0- and 2.7-fold increases in Cmax and AUC, respectively.

Elimination

Following an oral dose of ^14C-labeled clopidogrel in humans, approximately 50% of total radioactivity was excreted in urine and approximately 46% in feces over the 5 days post-dosing. After a single, oral dose of 75 mg, clopidogrel has a half-life of approximately 6 hours. The half-life of the active metabolite is about 30 minutes.

Drug Interactions

Clopidogrel is metabolized to its active metabolite in part by CYP2C19. Concomitant use of certain inhibitors of this enzyme results in reduced plasma concentrations of the active metabolite of clopidogrel and a reduction in platelet inhibition.

Proton Pump Inhibitors (PPI)

The effect of proton pump inhibitors (PPI) on the systemic exposure to the clopidogrel active metabolite following multiple doses of Plavix 75 mg evaluated in dedicated drug interaction studies is presented in Figure 1.

Figure 1: Exposure to Clopidogrel Active Metabolite Following Multiple Doses of Plavix 75 mg Alone or with Proton Pump Inhibitors (PPIs)

Pharmacodynamic and pharmacokinetic parameters measured in these studies showed that the interaction was highest with omeprazole and least with dexlansoprazole.

12.5 Pharmacogenomics

CYP2C19 is involved in the formation of both the active metabolite and the 2-oxo-clopidogrel intermediate metabolite. Clopidogrel active metabolite pharmacokinetics and antiplatelet effects, as measured by ex vivo platelet aggregation assays, differ according to CYP2C19 genotype. Genetic variants of other CYP450 enzymes may also affect the formation of clopidogrel's active metabolite.

The CYP2C19*1 allele corresponds to fully functional metabolism while the CYP2C19*2 and *3 alleles are nonfunctional. CYP2C19*2 and *3 account for the majority of reduced function alleles in white (85%) and Asian (99%) poor metabolizers. Other alleles associated with absent or reduced metabolism are less frequent, and include, but are not limited to, CYP2C19*4, *5, *6, *7, and *8. A patient with poor metabolizer status will possess two loss-of-function alleles as defined above. Published frequencies for poor CYP2C19 metabolizer genotypes are approximately 2% for whites, 4% for blacks and 14% for Chinese. Tests are available to determine a patient's CYP2C19 genotype.

A crossover study in 40 healthy subjects, 10 each in the four CYP2C19 metabolizer groups, evaluated pharmacokinetic and antiplatelet responses using 300 mg followed by 75 mg per day and 600 mg followed by 150 mg per day, each for a total of 5 days. Decreased active metabolite exposure and diminished inhibition of platelet aggregation were observed in the poor metabolizers as compared to the other groups. When poor metabolizers received the 600 mg/150 mg regimen, active metabolite exposure and antiplatelet response were greater than with the 300 mg/75 mg regimen (see Table 3). An appropriate dose regimen for this patient population has not been established in clinical outcome trials.

Table 3: Active Metabolite Pharmacokinetics and Antiplatelet Responses by CYP2C19 Metabolizer Status
 | Dose | Ultrarapid (n=10) | Extensive (n=10) | Intermediate (n=10) | Poor (n=10)
Cmax (ng/mL) | 300 mg (24 h) | 24 (10) | 32 (21) | 23 (11) | 11 (4)
 | 600 mg (24 h) | 36 (13) | 44 (27) | 39 (23) | 17 (6)
 | 75 mg (Day 5) | 12 (6) | 13 (7) | 12 (5) | 4 (1)
 | 150 mg (Day 5) | 16 (9) | 19 (5) | 18 (7) | 7 (2)
IPA (%) [Inhibition of platelet aggregation with 5mcM ADP; larger value indicates greater platelet inhibition] | 300 mg (24 h) | 40 (21) | 39 (28) | 37 (21) | 24 (26)
 | 600 mg (24 h) | 51 (28) | 49 (23) | 56 (22) | 32 (25)
 | 75 mg (Day 5) | 56 (13) | 58 (19) | 60 (18) | 37 (23)
 | 150 mg (Day 5) | 68 (18) | 73 (9) | 74 (14) | 61 (14)
VASP-PRI (%) [Vasodilator-stimulated phosphoprotein – platelet reactivity index; smaller value indicates greater platelet inhibition] | 300 mg (24 h) | 73 (12) | 68 (16) | 78 (12) | 91 (12)
 | 600 mg (24 h) | 51 (20) | 48 (20) | 56 (26) | 85 (14)
 | 75 mg (Day 5) | 40 (9) | 39 (14) | 50 (16) | 83 (13)
 | 150 mg (Day 5) | 20 (10) | 24 (10) | 29 (11) | 61 (18)
Values are mean (SD)

Some published studies suggest that intermediate metabolizers have decreased active metabolite exposure and diminished antiplatelet effects.

The relationship between CYP2C19 genotype and Plavix treatment outcome was evaluated in retrospective analyses of Plavix-treated subjects in CHARISMA (n=2428) and TRITON-TIMI 38 (n=1477), and in several published cohort studies. In TRITON-TIMI 38 and the majority of the cohort studies, the combined group of patients with either intermediate or poor metabolizer status had a higher rate of cardiovascular events (death, myocardial infarction, and stroke) or stent thrombosis compared to extensive metabolizers. In CHARISMA and one cohort study, the increased event rate was observed only in poor metabolizers.

13 NONCLINICAL TOXICOLOGY

13.1 Carcinogenesis, Mutagenesis, Impairment of Fertility

There was no evidence of tumorigenicity when clopidogrel was administered for 78 weeks to mice and 104 weeks to rats at dosages up to 77 mg/kg per day, which afforded plasma exposures >25 times that in humans at the recommended daily dose of 75 mg.

Clopidogrel was not genotoxic in four in vitro tests (Ames test, DNA-repair test in rat hepatocytes, gene mutation assay in Chinese hamster fibroblasts, and metaphase chromosome analysis of human lymphocytes) and in one in vivo test (micronucleus test by oral route in mice).

Clopidogrel was found to have no effect on fertility of male and female rats at oral doses up to 400 mg/kg per day (52 times the recommended human dose on a mg/m^2 basis).

14 CLINICAL STUDIES

14.1 Acute Coronary Syndrome

CURE

The CURE study included 12,562 patients with ACS without ST-elevation (UA or NSTEMI) and presenting within 24 hours of onset of the most recent episode of chest pain or symptoms consistent with ischemia. Patients were required to have either ECG changes compatible with new ischemia (without ST-elevation) or elevated cardiac enzymes or troponin I or T to at least twice the upper limit of normal. The patient population was largely Caucasian (82%) and included 38% women, and 52% patients ≥65 years of age.

Patients were randomized to receive Plavix (300-mg loading dose followed by 75 mg once daily) or placebo, and were treated for up to one year. Patients also received aspirin (75–325 mg once daily) and other standard therapies such as heparin. The use of GPIIb/IIIa inhibitors was not permitted for three days prior to randomization.

The number of patients experiencing the primary outcome (CV death, MI, or stroke) was 582 (9.3%) in the Plavix-treated group and 719 (11.4%) in the placebo-treated group, a 20% relative risk reduction (95% CI of 10%–28%; p < 0.001) for the Plavix-treated group (see Table 4).

Table 4: Outcome Events in the CURE Primary Analysis
Outcome | Plavix (+ aspirin) [Other standard therapies were used as appropriate.] | Placebo (+ aspirin) | Relative Risk Reduction (%) (95% CI)
 | (n=6259) | (n=6303)
Primary outcome (Cardiovascular death, MI, stroke) | 582 (9.3%) | 719 (11.4%) | 20% (10.3, 27.9) p < 0.001
All Individual Outcome Events: [The individual components do not represent a breakdown of the primary and co-primary outcomes, but rather the total number of subjects experiencing an event during the course of the study.]
CV death | 318 (5.1%) | 345 (5.5%) | 7% (-7.7, 20.6)
MI | 324 (5.2%) | 419 (6.6%) | 23% (11.0, 33.4)
Stroke | 75 (1.2%) | 87 (1.4%) | 14% (-17.7, 36.6)

Most of the benefit of Plavix occurred in the first two months, but the difference from placebo was maintained throughout the course of the trial (up to 12 months) (see Figure 2).

Figure 2: Cardiovascular Death, Myocardial Infarction, and Stroke in the CURE Study

In CURE, the use of Plavix was associated with a lower incidence of CV death, MI or stroke in patient populations with different characteristics, as shown in Figure 3. The benefits associated with Plavix were independent of the use of other acute and long-term cardiovascular therapies, including heparin/LMWH, intravenous glycoprotein IIb/IIIa (GPIIb/IIIa) inhibitors, lipid-lowering drugs, beta-blockers, and ACE-inhibitors. The efficacy of Plavix was observed independently of the dose of aspirin (75–325 mg once daily). The use of oral anticoagulants, non-study antiplatelet drugs, and chronic NSAIDs was not allowed in CURE.

Figure 3: Hazard Ratio for Patient Baseline Characteristics and On-Study Concomitant Medications/Interventions for the CURE Study

The use of Plavix in CURE was associated with a decrease in the use of thrombolytic therapy (71 patients [1.1%] in the Plavix group, 126 patients [2.0%] in the placebo group; relative risk reduction of 43%), and GPIIb/IIIa inhibitors (369 patients [5.9%] in the Plavix group, 454 patients [7.2%] in the placebo group, relative risk reduction of 18%). The use of Plavix in CURE did not affect the number of patients treated with CABG or PCI (with or without stenting), (2253 patients [36.0%] in the Plavix group, 2324 patients [36.9%] in the placebo group; relative risk reduction of 4.0%).

COMMIT

In patients with STEMI, the safety and efficacy of Plavix were evaluated in the randomized, placebo-controlled, double-blind study, COMMIT. COMMIT included 45,852 patients presenting within 24 hours of the onset of the symptoms of myocardial infarction with supporting ECG abnormalities (i.e., ST-elevation, ST-depression or left bundle-branch block). Patients were randomized to receive Plavix (75 mg once daily) or placebo, in combination with aspirin (162 mg per day), for 28 days or until hospital discharge, whichever came first.

The primary endpoints were death from any cause and the first occurrence of re-infarction, stroke or death.

The patient population included 28% women, 58% age ≥ 60 years (26% age ≥ 70 years), 55% patients who received thrombolytics, 68% who received ACE-inhibitors, and only 3% who underwent PCI.

As shown in Table 5 and Figure 4 and Figure 5 below, Plavix significantly reduced the relative risk of death from any cause by 7% (p=0.029), and the relative risk of the combination of re-infarction, stroke or death by 9% (p=0.002).

Table 5: Outcome Events in the COMMIT Analysis
Event | Plavix (+ aspirin) (N=22961) | Placebo (+ aspirin) (N=22891) | Odds ratio (95% CI) | p-value
Composite endpoint: Death, MI, or Stroke [The difference between the composite endpoint and the sum of death+non-fatal MI+non-fatal stroke indicates that 9 patients (2 clopidogrel and 7 placebo) suffered both a non-fatal stroke and a non-fatal MI.] | 2121 (9.2%) | 2310 (10.1%) | 0.91 (0.86, 0.97) | 0.002
Death | 1726 (7.5%) | 1845 (8.1%) | 0.93 (0.87, 0.99) | 0.029
Non-fatal MI [Non-fatal MI and non-fatal stroke exclude patients who died (of any cause).] | 270 (1.2%) | 330 (1.4%) | 0.81 (0.69, 0.95) | 0.011
Non-fatal Stroke | 127 (0.6%) | 142 (0.6%) | 0.89 (0.70, 1.13) | 0.33

Figure 4: Cumulative Event Rates for Death in the COMMIT Study [All treated patients received aspirin.]

Figure 5: Cumulative Event Rates for the Combined Endpoint Re-Infarction, Stroke or Death in the COMMIT Study [All treated patients received aspirin.]

The effect of Plavix did not differ significantly in various pre-specified subgroups as shown in Figure 6. The effect was also similar in non-prespecified subgroups including those based on infarct location, Killip class or prior MI history (see Figure 7). Such subgroup analyses should be interpreted cautiously.

Figure 6: Effects of Adding Plavix to Aspirin on the Combined Primary Endpoint across Baseline and Concomitant Medication Subgroups for the COMMIT Study

* Three similar-sized prognostic index groups were based on absolute risk of primary composite outcome for each patient calculated from baseline prognostic variables (excluding allocated treatments) with a Cox regression model.

Figure 7: Effects of Adding Plavix to Aspirin in the Non-Prespecified Subgroups in the COMMIT Study

14.2 Recent Myocardial Infarction, Recent Stroke, or Established Peripheral Arterial Disease

CAPRIE

The CAPRIE trial was a 19,185-patient, 304-center, international, randomized, double-blind, parallel-group study comparing Plavix (75 mg daily) to aspirin (325 mg daily). The patients randomized had: 1) recent histories of myocardial infarction (within 35 days); 2) recent histories of ischemic stroke (within 6 months) with at least a week of residual neurological signs; or 3) established peripheral arterial disease. Patients received randomized treatment for an average of 1.6 years (maximum of 3 years).

The trial's primary outcome was the time to first occurrence of new ischemic stroke (fatal or not), new myocardial infarction (fatal or not), or other vascular death. Deaths not easily attributable to nonvascular causes were all classified as vascular.

Table 6: Outcome Events in the CAPRIE Primary Analysis
 | Plavix | aspirin
Patients | n=9599 | n=9586
Ischemic stroke (fatal or not) | 438 (4.6%) | 461 (4.8%)
MI (fatal or not) | 275 (2.9%) | 333 (3.5%)
Other vascular death | 226 (2.4%) | 226 (2.4%)
Total | 939 (9.8%) | 1020 (10.6%)

As shown in Table 6, Plavix was associated with a lower incidence of outcome events, primarily MI. The overall relative risk reduction (9.8% vs. 10.6%) was 8.7%, p=0.045. Similar results were obtained when all-cause mortality and all-cause strokes were counted instead of vascular mortality and ischemic strokes (risk reduction 6.9%). In patients who survived an on-study stroke or myocardial infarction, the incidence of subsequent events was lower in the Plavix group.

The curves showing the overall event rate are shown in Figure 8. The event curves separated early and continued to diverge over the 3-year follow-up period.

Figure 8: Fatal or Non-Fatal Vascular Events in the CAPRIE Study

The statistical significance favoring Plavix over aspirin was marginal (p=0.045). However, because aspirin is itself effective in reducing cardiovascular events in patients with recent myocardial infarction or stroke, the effect of Plavix is substantial.

The CAPRIE trial included a population that was randomized on the basis of 3 entry criteria. The efficacy of Plavix relative to aspirin was heterogeneous across these randomized subgroups (p=0.043). It is not clear whether this difference is real or a chance occurrence. Although the CAPRIE trial was not designed to evaluate the relative benefit of Plavix over aspirin in the individual patient subgroups, the benefit appeared to be strongest in patients who were enrolled because of peripheral vascular disease (especially those who also had a history of myocardial infarction) and weaker in stroke patients. In patients who were enrolled in the trial on the sole basis of a recent myocardial infarction, Plavix was not numerically superior to aspirin.

14.3 Lack of Established Benefit of Plavix plus Aspirin in Patients with Multiple Risk Factors or Established Vascular Disease

CHARISMA

The CHARISMA trial was a 15,603 subject, randomized, double-blind, parallel group study comparing Plavix (75 mg daily) to placebo for prevention of ischemic events in patients with vascular disease or multiple risk factors for atherosclerosis. All subjects were treated with aspirin 75–162 mg daily. The mean duration of treatment was 23 months. The study failed to demonstrate a reduction in the occurrence of the primary endpoint, a composite of CV death, MI, or stroke. A total of 534 (6.9%) patients in the Plavix group versus 573 (7.4%) patients in the placebo group experienced a primary outcome event (p=0.22). Bleeding of all severities was more common in the subjects randomized to Plavix.

16 HOW SUPPLIED/STORAGE AND HANDLING

Plavix (clopidogrel bisulfate) 75 mg tablets are available as pink, round, biconvex, film-coated tablets debossed with "75" on one side and "1171" on the other. Tablets are provided as follows:

Bottles of 30 | NDC 54868-4070-0
Bottles of 60 | NDC 54868-4070-2
Bottles of 90 | NDC 54868-4070-1

STORAGE AND HANDLING

Store at 25° C (77° F); excursions permitted to 15°–30° C (59°–86° F) [see USP Controlled Room Temperature].

17 PATIENT COUNSELING INFORMATION

[See Medication Guide (17.6)]

17.1 Benefits and Risks

- Summarize the effectiveness features and potential side effects of Plavix.
- Tell patients to take Plavix exactly as prescribed.
- Remind patients not to discontinue Plavix without first discussing it with the physician who prescribed Plavix.

17.2 Bleeding

Inform patients that they:

- will bruise and bleed more easily.
- will take longer than usual to stop bleeding.
- should report any unanticipated, prolonged, or excessive bleeding, or blood in their stool or urine.

17.3 Other Signs and Symptoms Requiring Medical Attention

- Inform patients that TTP is a rare but serious condition that has been reported with Plavix and other drugs in this class of drugs.
- Instruct patients to get prompt medical attention if they experience any of the following symptoms that cannot otherwise be explained: fever, weakness, extreme skin paleness, purple skin patches, yellowing of the skin or eyes, or neurological changes.

17.4 Invasive Procedures

Instruct patients to:

- inform physicians and dentists that they are taking Plavix before any invasive procedure is scheduled.
- tell the doctor performing the invasive procedure to talk to the prescribing health care professional before stopping Plavix.

17.5 Concomitant Medications

Ask patients to list all prescription medications, over-the-counter medications, or dietary supplements they are taking or plan to take, including prescription or over-the-counter proton pump inhibitors (e.g., omeprazole), warfarin or NSAIDs [see Warnings and Precautions (5)].

Medication Guide
Plavix® (PLAV-iks)
(clopidogrel bisulfate)
tablets

Read this Medication Guide before you start taking Plavix and each time you get a refill. There may be new information. This Medication Guide does not take the place of talking with your doctor about your medical condition or your treatment.

What is the most important information I should know about Plavix?

1. Plavix may not work as well in people who:
  - have certain genetic factors that affect how the body breaks down Plavix. Your doctor may do genetic tests to make sure Plavix is right for you.
  - take certain medicines, especially omeprazole (Prilosec®) or esomeprazole (Nexium®). Your doctor may change the medicine you take for stomach acid problems while you take Plavix.
2. Plavix can cause bleeding which can be serious and can sometimes lead to death. Plavix is a blood thinner medicine that lowers the chance of blood clots forming in your body. While you take Plavix:
  - you may bruise and bleed more easily
  - you are more likely to have nose bleeds
  - it will take longer for any bleeding to stop

Call your doctor right away if you have any of these signs or symptoms of bleeding:

- unexpected bleeding or bleeding that lasts a long time
- blood in your urine (pink, red or brown urine)
- red or black stools (looks like tar)
- bruises that happen without a known cause or get larger
- cough up blood or blood clots
- vomit blood or your vomit looks like coffee grounds

Do not stop taking Plavix without talking to the doctor who prescribes it for you. People who are treated with a stent, and stop taking Plavix too soon, have a higher risk of getting a blood clot on the stent, having a heart attack, or dying. If you must stop Plavix because of bleeding, your risk of a heart attack may be higher.

What is Plavix?

Plavix is a prescription medicine used to treat people who have any of the following:

- chest pain due to heart problems
- poor circulation in their legs (peripheral arterial disease)
- a heart attack
- a stroke

Plavix is used alone or with aspirin to lower your chance of having another serious problem with your heart or blood vessels such as heart attack, stroke, or blood clot that can lead to death.

Platelets are blood cells that help your blood clot normally. Plavix helps to prevent platelets from sticking together and forming a clot that can block an artery.

It is not known if Plavix is safe and effective in children.

Who should not take Plavix?

Do not take Plavix if you:

- currently have a condition that causes bleeding, such as a stomach ulcer
- are allergic to clopidogrel or other ingredients in Plavix. See the end of this leaflet for a complete list of ingredients in Plavix.

What should I tell my doctor before taking Plavix?

Before you take Plavix, tell your doctor if you:

- have a history of bowel (gastrointestinal) or stomach ulcers
- have a history of bleeding problems
- plan to have surgery or a dental procedure. See "How should I take Plavix?"
- are pregnant or plan to become pregnant. It is not known if Plavix will harm your unborn baby
- are breastfeeding or plan to breastfeed. It is not known if Plavix passes into your breast milk. You and your doctor should decide if you will take Plavix or breastfeed. You should not do both without talking to your doctor.

Tell all of your doctors and your dentist that you are taking Plavix. They should talk to the doctor who prescribed Plavix for you before you have any surgery or invasive procedure.

Tell your doctor about all the medicines you take, including prescription, non-prescription medicines, vitamins and herbal supplements.

Plavix may affect the way other medicines work, and other medicines may affect how Plavix works. See "What is the most important information I should know about Plavix?"

Taking Plavix with certain other medicines may increase your risk of bleeding. Especially tell your doctor if you take:

- aspirin, especially if you have had a stroke. Always talk to your doctor about whether you should take aspirin along with Plavix to treat your condition.
- Non-steroidal anti-inflammatory drugs (NSAIDs). Ask your doctor or pharmacist for a list of NSAID medicines if you are not sure.
- warfarin (Coumadin®, Jantoven®)

Know the medicines you take. Keep a list of them to show your doctor or pharmacist when you get a new medicine.

How should I take Plavix?

- Take Plavix exactly as your doctor tells you.
- Do not change your dose or stop taking Plavix without talking to your doctor first. Stopping Plavix may increase your risk of heart attack or stroke.
- Take Plavix with aspirin as instructed by your doctor.
- You can take Plavix with or without food.
- If you miss a dose, take Plavix as soon as you remember. If it is almost time for your next dose, skip the missed dose. Take the next dose at your regular time. Do not take 2 doses of Plavix at the same time unless your doctor tells you to.
- If you take too much Plavix, call your doctor or go to the nearest emergency room right away.
- Talk with your doctor about stopping your Plavix before you have surgery. Your doctor may tell you to stop taking Plavix at least 5 days before you have surgery to avoid excessive bleeding during surgery.

What are the possible side effects of Plavix?

Plavix can cause serious side effects including:

- See "What is the most important information I should know about Plavix?"
- A blood clotting problem called Thrombotic Thrombocytopenic Purpura (TTP). TTP can happen with Plavix, sometimes after a short time (less than 2 weeks). TTP is a blood clotting problem where blood clots form in blood vessels; and can happen anywhere in the body. TTP needs to be treated in a hospital right away, because it may cause death. Get medical help right away if you have any of these symptoms and they can not be explained by another medical condition:
  - purplish spots (called purpura) on the skin or in the mouth (mucous membranes) due to bleeding under the skin
  - your skin or the whites of your eyes are yellow (jaundice)
  - you feel tired or weak
  - your skin looks very pale
  - fever
  - fast heart rate or feeling short of breath
  - headache
  - speech changes
  - confusion
  - coma
  - stroke
  - seizure
  - low amount of urine, or urine that is pink or has blood in it
  - stomach area (abdominal) pain
  - nausea, vomiting, or diarrhea
  - vision changes

Tell your doctor if you have any side effect that bothers you or that does not go away.

These are not all the possible side effects of Plavix. For more information, ask your doctor or pharmacist.

Call your doctor for medical advice about side effects. You may report side effects to FDA at 1-800-FDA-1088.

How should I store Plavix?

- Store Plavix at 59°F to 86°F (15°C to 30°C).

Keep Plavix and all medicines out of the reach of children.

General information about Plavix

Medicines are sometimes used for purposes other than those listed in a Medication Guide. Do not take Plavix for a condition for which it was not prescribed. Do not give Plavix to other people, even if they have the same symptoms that you have. It may harm them.

This Medication Guide summarizes the most important information about Plavix. If you would like more information, talk to your doctor. Ask your doctor or pharmacist for information about Plavix that was written for healthcare professionals.

For more information, go to www.sanofi-aventis.us or www.bms.com or call 1-800-321-1335.

What are the ingredients in Plavix?

Active ingredient: clopidogrel bisulfate

Inactive ingredients:

Tablet: hydrogenated castor oil, hydroxypropylcellulose, mannitol, microcrystalline cellulose, polyethylene glycol 6000

Film coating: ferric oxide, hypromellose 2910, lactose monohydrate, titanium dioxide, triacetin, Carnauba wax

This Medication Guide has been approved by the U.S. Food and Drug Administration.

Revised December 2011

Distributed by:
Bristol-Myers Squibb/Sanofi Pharmaceuticals Partnership
Bridgewater, NJ 08807

Plavix® is a registered trademark of sanofi-aventis.
Coumadin® is a registered trademark of Bristol-Myers Squibb Pharma Company.
Prilosec® is a registered trademark of AstraZeneca.
Jantoven® is a registered trademark of USL Pharma.

Relabeling and Repackaging by:
Physicians Total Care, Inc.
Tulsa, Oklahoma 74146

PRINCIPAL DISPLAY PANEL - 75 mg Bottle Label

Plavix®
(clopidogrel bisulfate)

75 mg

Dispense with
Medication Guide

Rx only